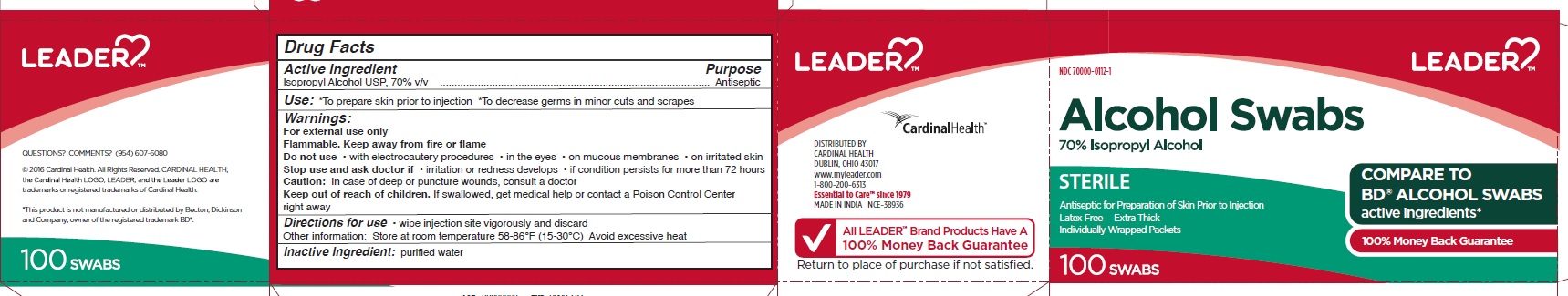 DRUG LABEL: Alcohol Prep
NDC: 70000-0112 | Form: SWAB
Manufacturer: Cardinal Health
Category: otc | Type: HUMAN OTC DRUG LABEL
Date: 20251023

ACTIVE INGREDIENTS: ISOPROPYL ALCOHOL 70 mL/100 mL
INACTIVE INGREDIENTS: WATER

Leader Alcohol Prep Pads

Active Ingredients

Isopropyl Alcohol USP, 70% v/v

Purpose

Antiseptic

Uses

- To prepare skin prior to injection
- To decrease germs in minor cuts and scrapes

Warnings

For external use only

Flammable. Keep away from fire or flame

Do not use

- with electrocautery procedures
- in the eyes
- on mucous membranes
- on irritated skin

Stop use and ask doctor if

- irritation or redness develops
- if condition persists for more than 72 hours

Caution

In case of deep or puncture wounds, consult a doctor

Keep out of reach of children

If swallowed, get medical help or contact a Poison Control Center right away

Directions for use

- wipe injection site vigorously and discard

Other Information

- Store at room temperature 59-86⁰F (15-30⁰C)
- Avoid excessive heat

Inactive Ingredient

purified water

Principal Display Panel

NDC 70000-0112-1

LEADER

Alcohol Swabs

70% Isopropyl Alcohol

STERILE

Antiseptic for Preparation of Skin Prior to Injection

Latex Free

Extra Thick

Individually Wrapped Packets

COMPARE TO BD ALCOHOL SWABS

active ingredients*

100% Money Back Guarantee

100 SWABS